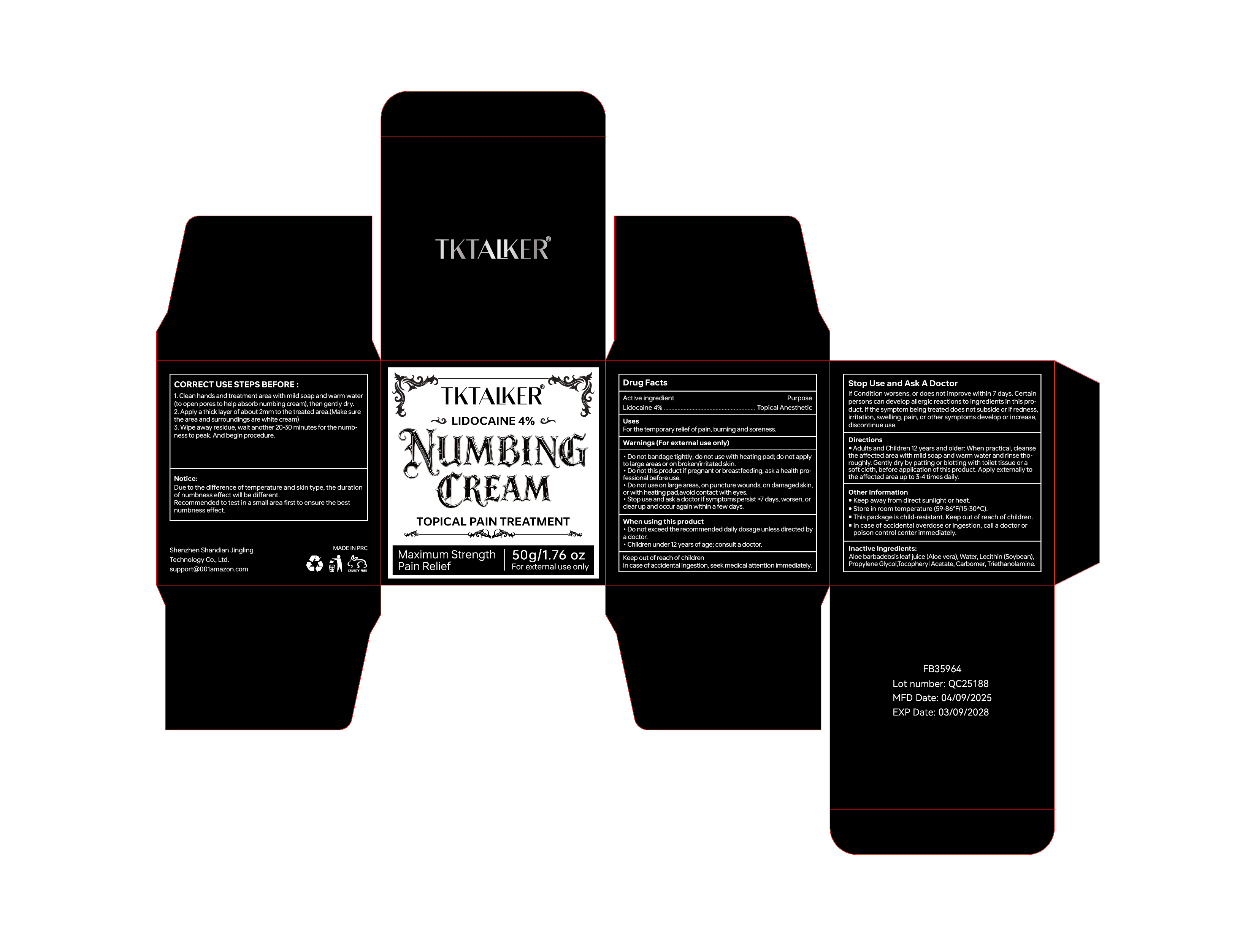 DRUG LABEL: TKTALKER NUMBING
NDC: 83804-113 | Form: CREAM
Manufacturer: Shenzhen Shandian Jingling Technology Co., Ltd.
Category: otc | Type: HUMAN OTC DRUG LABEL
Date: 20250829

ACTIVE INGREDIENTS: LIDOCAINE 4 g/100 g
INACTIVE INGREDIENTS: PROPYLENE GLYCOL; ALOE VERA WHOLE; HYDROGENATED SOYBEAN LECITHIN; CARBOMER; WATER; .ALPHA.-TOCOPHEROL ACETATE; TRIETHANOLAMINE

83804-113

Active Ingredient

Lidocaine 4%

Purpose

Topical Anesthetic

Use

For the temporary relief of pain, burning and soreness.

Warnings

Warnings (For external use only)
●Do not bandage tightly; do not use with heating pad; do not apply to large areas or on broken/irritated skin.
●Do not this product if pregnant or breastfeeding, ask a health professional before use.
●Do not use on large areas, on puncture wounds, on damaged skin, or with heating pad,avoid contact with eyes.
●Stop use and ask a doctor if symptoms persist >7 days, worsen, or clear up and occur again within a few days.

Do not use

●Do not bandage tightly; do not use with heating pad; do not apply to large areas or on broken/irritated skin.
●Do not this product if pregnant or breastfeeding, ask a health professional before use.
●Do not use on large areas, on puncture wounds, on damaged skin, or with heating pad,avoid contact with eyes.

When Using

When using this product
●Do not exceed the recommended daily dosage unless directed by a doctor.
●Children under 12 years of age; consult a doctor.

Stop Use

If Condition worsens, or does not improve within 7 days. Certain persons can develop allergic reactions to ingredients in this product. If the symptom being treated does not subside or if redness, irritation, swelling, pain, or other symptoms develop or increase, discontinue use.
●Stop use and ask a doctor if symptoms persist >7 days, worsen, or clear up and occur again within a few days.

Ask Doctor

●Stop use and ask a doctor if symptoms persist >7 days, worsen, or clear up and occur again within a few days.

Keep Out Of Reach Of Children

In case of accidental ingestion, seek medical attention immediately.

Directions

●Adults and Children 12 years and older: When practical, cleanse the affected area with mild soap and warm water and rinse thoroughly. Gently dry by patting or blotting with toilet tissue or a soft cloth, before application of this product. Apply externally to the affected area up to 3-4 times daily.

Other information

●Keep away from direct sunlight or heat.
●Store in room temperature (59-86°F/15-30*C).
■ This package is child-resistant. Keep out of reach of children.
■ In case of accidental overdose or ingestion, call a doctor or poison control center immediately.

CORRECT USE STEPS BEFORE :
1. Clean hands and treatment area with mild soap and warm water (to open pores to help absorb numbing cream), then gently dry.
2. Apply a thick layer of about 2mm to the treated area.(Make sure the area and surroundings are white cream)
3. Wipe away residue, wait another 20-30 minutes for the numbness to peak. And begin procedure.

Notice:
Due to the difference of temperature and skin type, the durationof numbness effect will be different.Recommended to test in a small area first to ensure the bestnumbness effect.

Inactive ingredients

Aloe barbadebsis leaf juice (Aloe vera), Water, Lecithin (Soybean), Propylene Glycol,Tocopheryl Acetate, Carbomer, Triethanolamine.

Questions

support@001amazon.com